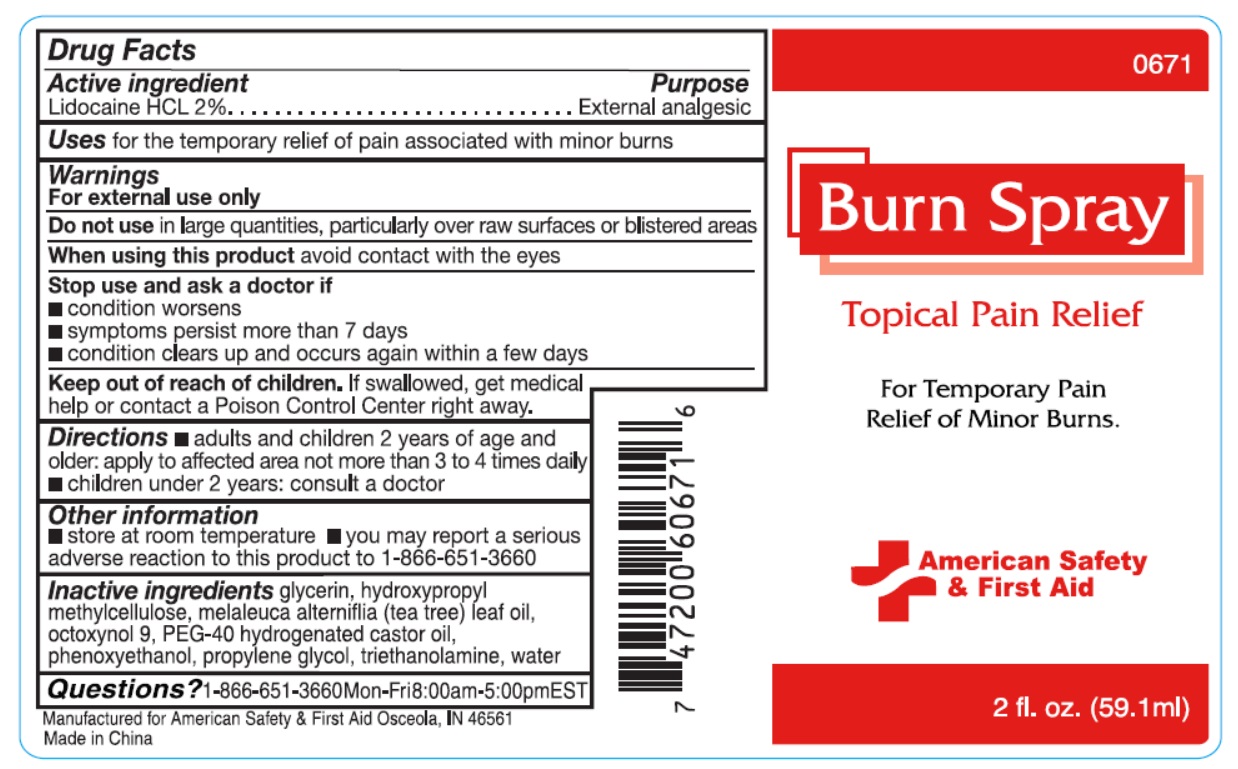 DRUG LABEL: American Safety First Aid
NDC: 71927-012 | Form: SPRAY
Manufacturer: Orazen Inc
Category: otc | Type: HUMAN OTC DRUG LABEL
Date: 20240115

ACTIVE INGREDIENTS: LIDOCAINE HYDROCHLORIDE 20 mg/1 mL
INACTIVE INGREDIENTS: HYPROMELLOSES; WATER; GLYCERIN; OCTOXYNOL 9; TEA TREE OIL; POLYOXYL 40 HYDROGENATED CASTOR OIL; PHENOXYETHANOL; PROPYLENE GLYCOL; TROLAMINE

71927-012 American Safety & First Aid Burn Spray

Active ingredient

Lidocaine HCL 2%

Purpose

External analgesic

Uses

for the temporary relief of pain associated with minor burns

Warnings

For external use only

Do not use

in large quantities, particularly over raw surfaces or blistered areas

When using this product

avoid contact with the eyes

Stop use and ask a doctor if

- condition worsens
- symptoms persist more than 7 days
- condition clears up and occurs again within a few days

Keep out of reach of children.

If swallowed, get medical help or contact a Poison Control Center right away.

Directions

- adults and children 2 years of age and older: apply to affected area not more than 3 to 4 times daily
- children under 2 years: consult a doctor

Other information

- store at room temperature
- you may report a serious adverse reaction to this product to 1-866-651-3660

Inactive ingredients

glycerin, hydroxypropyl methylcellulose, melaleuca alterniflia (tea tree) leaf oil, octoxynol 9, PEG-40 hydrogenated castor oil, phenoxyethanol, propylene glycol, triethanolamine, water

Questions?

1-866-651-3660
Mon-Fri 8:00am-5:00pm EST